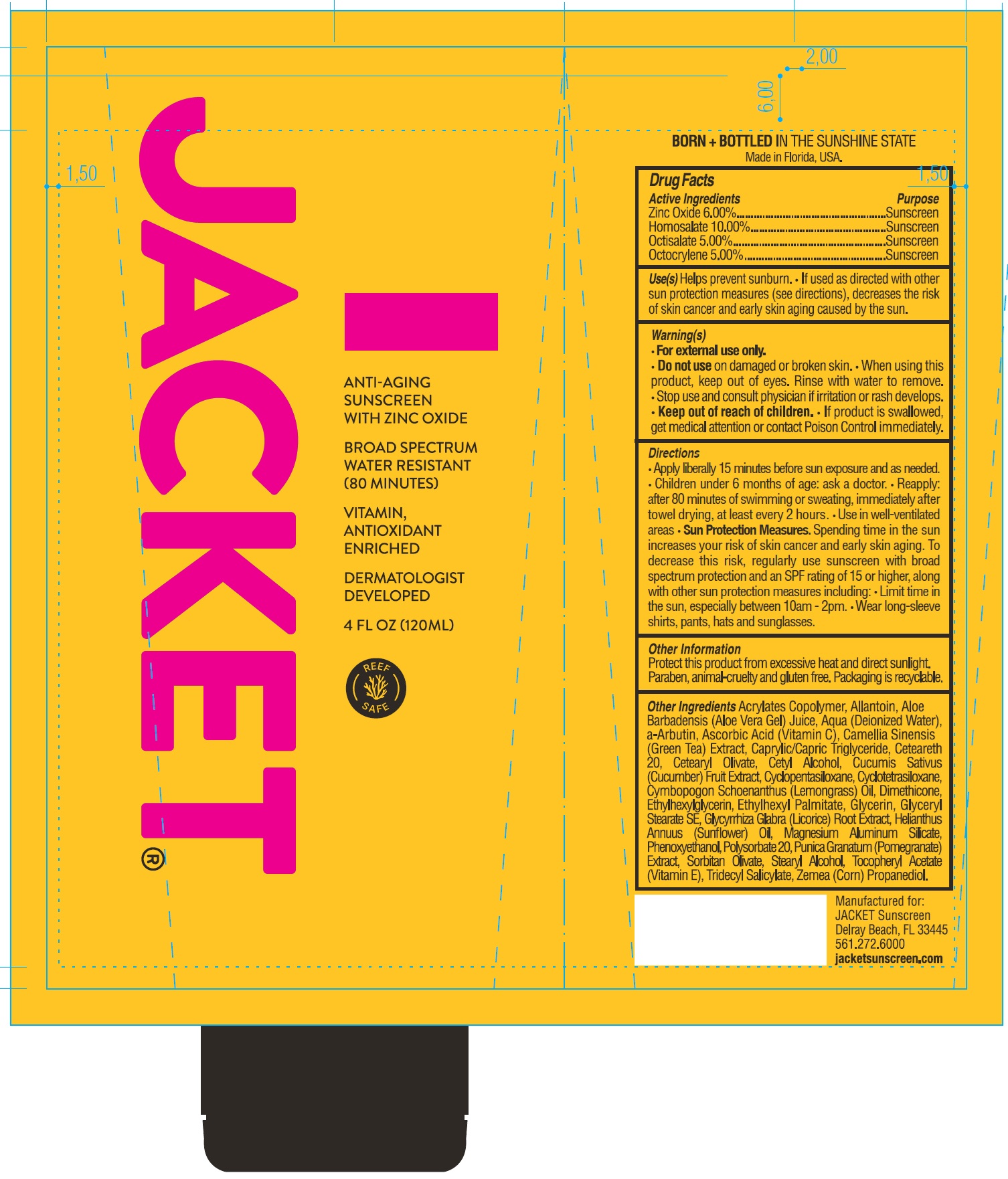 DRUG LABEL: JACKET SPF-50 Broad Spectrum Sunscreen
NDC: 71070-868 | Form: LOTION
Manufacturer: BALSHI MD DERMACEUTICALS
Category: otc | Type: HUMAN OTC DRUG LABEL
Date: 20240829

ACTIVE INGREDIENTS: ZINC OXIDE 60 mg/1 mL; HOMOSALATE 100 mg/1 mL; OCTISALATE 50 mg/1 mL; OCTOCRYLENE 50 mg/1 mL
INACTIVE INGREDIENTS: BUTYL ACRYLATE/METHYL METHACRYLATE/METHACRYLIC ACID COPOLYMER (18000 MW); ALLANTOIN; ALOE VERA LEAF; WATER; ASCORBIC ACID; GREEN TEA LEAF; MEDIUM-CHAIN TRIGLYCERIDES; POLYOXYL 20 CETOSTEARYL ETHER; CETEARYL OLIVATE; CETYL ALCOHOL; CUCUMBER; CYCLOMETHICONE 5; CYCLOMETHICONE 4; CYMBOPOGON CITRATUS LEAF; DIMETHICONE; ETHYLHEXYLGLYCERIN; ETHYLHEXYL PALMITATE; GLYCERIN; GLYCERYL MONOSTEARATE; LICORICE; HELIANTHUS ANNUUS FLOWERING TOP; MAGNESIUM ALUMINUM SILICATE; PHENOXYETHANOL; POLYSORBATE 20; POMEGRANATE; SORBITAN OLIVATE; STEARYL ALCOHOL; .ALPHA.-TOCOPHEROL ACETATE; TRIDECYL SALICYLATE; CORN; PROPANEDIOL

JACKET SPF-50 Broad Spectrum Sunscreen

Active Ingredients

Zinc Oxide 6.00%

Homosalate 10.00%

Octisalate 5.00%

Octocrylene 5.00%

Purpose

Sunscreen

Uses

Helps prevent sunburn

- If used as directed with other sun protection measures (see directions), decreases the risk of skin cancer and early skin aging caused by the sun.

Warnings

- For external use only.

Do not use

on damaged or broken skin.

When using this product

keep out of eyes. Rinse with water to remove.

Stop use and consult physician

if irritation or rash develops

Keep out of reach of children.

If product is swallowed, get medical attention or contact poison control center immediately.

Directions

• Apply liberally 15 minutes before sun exposure • Reapply: *At least every 2 hours *Immediately after swimming, sweating or towel drying Spending time in the sun increases your risk of skin cancer and early skin aging. To decrease this risk, regularly use sunscreen with broad spectrum protection and an SPF rating of 15 or higher, along with other sun protection measures including: *Limit time in the sun, especially between 10am -2pm *Wear long sleeve shirts, pants, hats and sunglasses *For children under 6 months, consult a physician.
Sun Protection Measures:

Other Ingredients

Acrylates Copolymer, Allantoin, Aloe Barbadensis (Aloe Vera Gel) Juice, Aqua (Deionized Water), a-Arbutin, Ascorbic Acid (Vitamin C), Camellia Sinensis (Green Tea) Extract, Caprylic/Capric Triglyceride, Ceteareth 20, Cetearyl Olivate, Cetyl Alcohol, Cucumis Sativus (Cucumber) Fruit Extract, Cyclopentasiloxane, Cyclotetrasiloxane, Cymbopogon Schoenanthus (Lemongrass) Oil, Dimethicone, Ethylhexylglycerin, Ethylhexyl Palmitate, Glycerin, Glyceryl Stearate, Glycyrrhiza Glabra (Licorice) Root Extract, Helianthus Annuus (Sunflower) Oil, Magnesium Aluminum Silicate, Phenoxyethanol, Polysorbate 20, Punica Granatum (Pomegranate) Extract, Sorbitan Olivate, Stearyl Alcohol, Tocopheryl Acetate (Vitamin E), Tridecyl Salicylate, Zema (Corn) Propanediol

Other Information

Protect this product from excessive heat and direct sunlight.